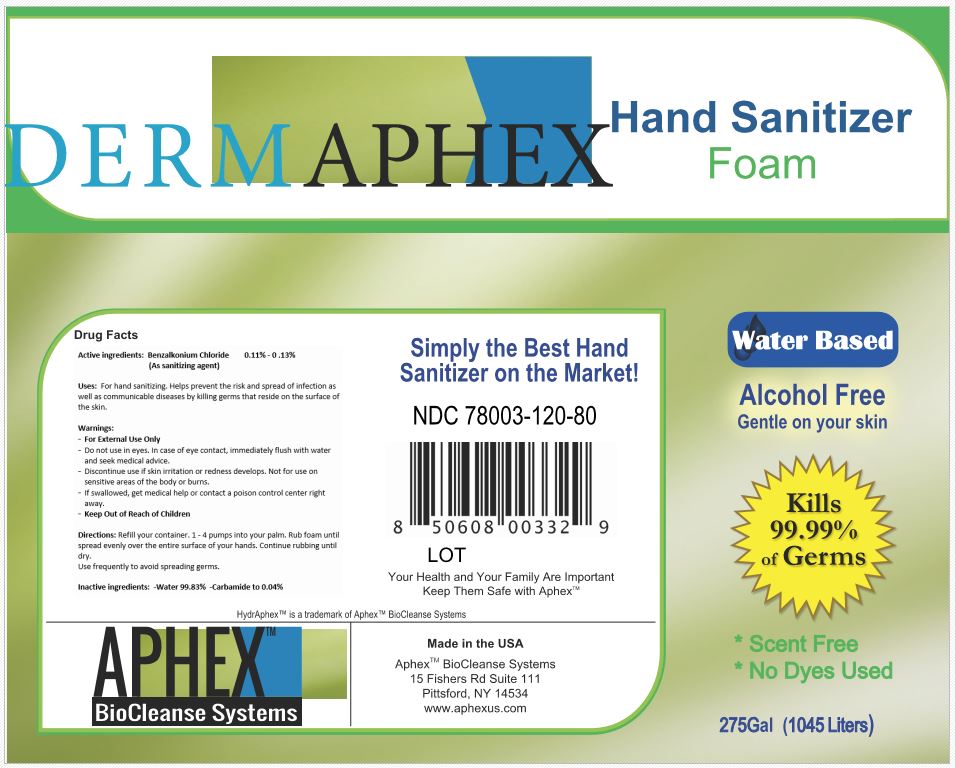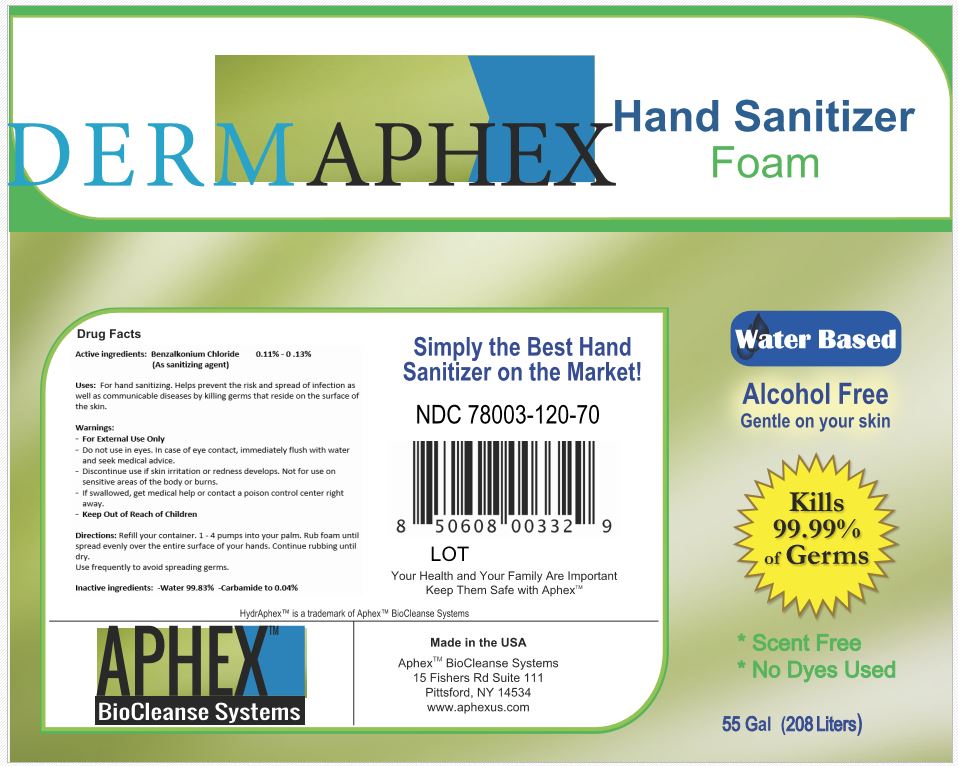 DRUG LABEL: DermAphex Hand Sanitizer
NDC: 78003-120 | Form: SOLUTION
Manufacturer: Aphex Biocleanse Systems, Inc
Category: otc | Type: HUMAN OTC DRUG LABEL
Date: 20220117

ACTIVE INGREDIENTS: BENZALKONIUM CHLORIDE 0.0013 g/1 mL
INACTIVE INGREDIENTS: UREA 0.0006 g/1 mL; WATER 1 mL/1 mL

DermAphex Hand Sanitizer

Dosage and Administration

Directions: Refill your container. 1 - 4 pumps into your palm. Rub foam until spread evenly over the entire surface of your hands. Continue rubbing until dry.

Use frequently to avoid spreading germs.

Warnings

For External Use Only
Do not use in eyes. In case of eye contact, immediately flush with water and seek medical advice.
Discontinue use if skin irritation or redness develops. Not for use on sensitive areas of the body or burns.
If swallowed, get medical help or contact a poison control center right away.
Keep Out of Reach of Children

Inactive Ingredient

Inactive ingredients: -Water 99.83% -Carbamide to 0.04%

Indications and Usage

Uses: For hand sanitizing. Helps prevent the risk and spread of infection as well as communicable diseases by killing germs that reside on the surface of the skin.

Keep out of Reach of Children

Warnings:

For External Use Only
Do not use in eyes. In case of eye contact, immediately flush with water and seek medical advice.
Discontinue use if skin irritation or redness develops. Not for use on sensitive areas of the body or burns.
If swallowed, get medical help or contact a poison control center right away.
Keep Out of Reach of Children

Purpose

Active ingredients: Benzalkonium Chloride 0.11% - 0 .13%

(As sanitizing agent)

Active Ingredient

Active ingredients: Benzalkonium Chloride 0.11% - 0 .13%

(As sanitizing agent)